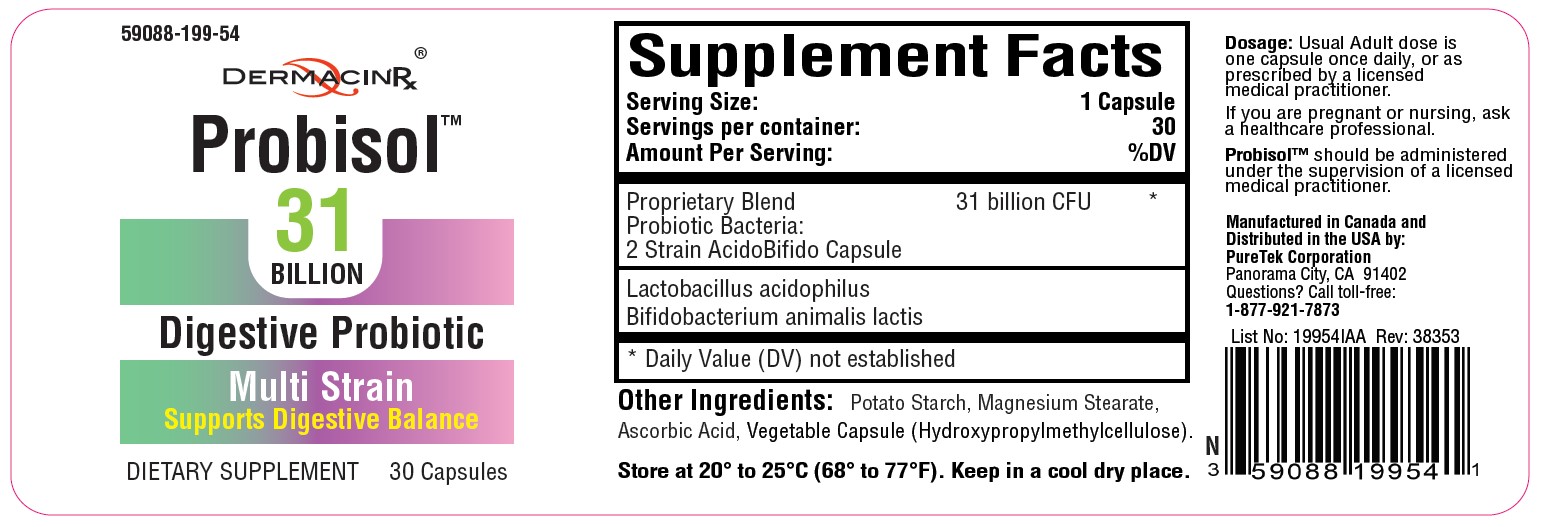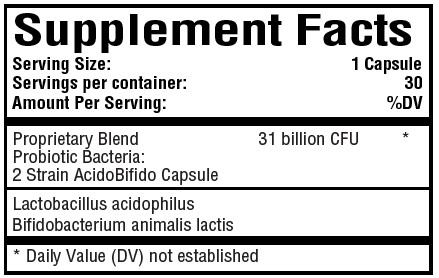 DRUG LABEL: Probisol
NDC: 59088-199 | Form: CAPSULE
Manufacturer: PureTek Corporation
Category: other | Type: DIETARY SUPPLEMENT
Date: 20211129

ACTIVE INGREDIENTS: LACTOBACILLUS ACIDOPHILUS 16000000000 [CFU]/1 1; BIFIDOBACTERIUM ANIMALIS LACTIS 15000000000 [CFU]/1 1

Probisol™

STATEMENT OF IDENTITY

Probisol™

Other Ingredients: Potato Starch, Magnesium Stearate, Ascorbic Acid, Vegetable Capsule (Hydroxypropylmethylcellulose).

Probisol™ is an orally administered prescription probiotic formulation for the clinical dietary management of suboptimal nutritional status in patients where advanced supplementation is required and nutritional supplementation in physiologically stressful conditions for maintenance of good health is needed.
Probisol™ should be administered under the supervision of a licensed medical practitioner.
Probisol™ is manufactured in accordance with Current Good Manufacturing Practice for foods, using ingredients that have been approved by the U.S. Food and Drug Administration (FDA) as food additives or are Generally Recognized as Safe (GRAS) for their intended use.

DOSAGE

Usual Adult dose is one capsule once daily, or as prescribed by a licensed medical practitioner.
If you are pregnant or nursing, ask a healthcare professional.

Probisol™ should be administered under the supervision of a licensed medical practitioner.

SAFE HANDLING

This product is contraindicated in patients with a known hypersensitivity to any of the ingredients.

Probisol™ should only be used under the direction and supervision of a licensed medical practitioner. Use with caution in patients that may have a medical condition, are pregnant, lactating, trying to conceive, under the age of 18, or taking medications.

KEEP OUT OF REACH OF CHILDREN

STORAGE

Store at 20° to 25°C (68° to 77°F).
Keep in a cool dry place.

HOW SUPPLIED HEALTH CLAIM

Probisol™, Probiotic

Dietary Supplement

NHRIC: 59088-199-54 *

Bottles contain 30 Capsules

Manufactured in Canada and
Distributed in the USA by:
PureTek Corporation
Panorama City, CA 91402
Questions? Call toll-free:
1-877-921-7873

*Does not represent these product codes to be National Drug Codes (NDC). Product codes are formatted according to standard industry practice, to meet the formatting requirement by pedigree reporting and supply-chain control including pharmacies.

† The most appropriate way to ensure pedigree reporting consistent with these regulatory guidelines and safety monitoring is to dispense this product by prescription. This is not an Orange Book product. This product may be administered only under a physician’s supervision and all prescriptions using this product shall be pursuant to state statutes as applicable. The ingredients, indication or claims of this product are not to be construed to be drug claims.